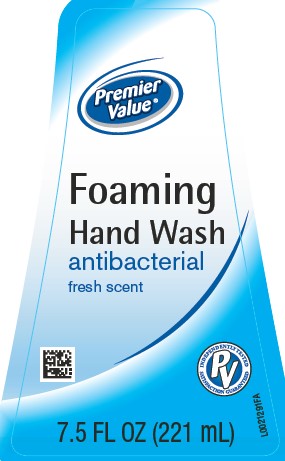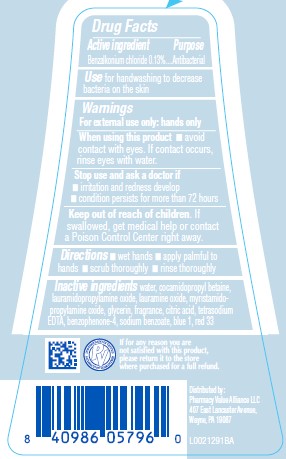 DRUG LABEL: Benzalkonium chloride
NDC: 68016-866 | Form: LIQUID
Manufacturer: Pharmacy Value Alliance, LLC
Category: otc | Type: HUMAN OTC DRUG LABEL
Date: 20260205

ACTIVE INGREDIENTS: BENZALKONIUM CHLORIDE 1.3 mg/1 mL
INACTIVE INGREDIENTS: WATER; COCAMIDOPROPYL BETAINE; LAURAMIDOPROPYLAMINE OXIDE; LAURAMINE OXIDE; MYRISTAMIDOPROPYLAMINE OXIDE; GLYCERIN; CITRIC ACID MONOHYDRATE; EDETATE SODIUM; SULISOBENZONE; SODIUM BENZOATE; FD&C BLUE NO. 1; D&C RED NO. 33

Premier Value 628.002/628AD-AF
Antibacterial Foaming Hand Wash

Active ingredient

Benzalkonium chloride 0.13%

Purpose

Antibacterial

Use

for handwashing to decrease bacteria on the skin

Warnings

For external use only: hands only

When using this product

- avoid contact with eyes. If contact occurs, rinse eyes thoroughly with water.

Stop use and ask a doctor if

- irritation and redness develop
- condition persists for more than 72 hours

Keep out of reach of children.

If swallowed, get medical help or contact a Poison Control Center right away.

Directions

- wet hands
- apply palmful to hands
- scrub thoroughly
- rinse thoroughly

Inactive ingredients

water, cocamidopropyl betaine, lauramidopropylamine oxide, lauramine oxide, myristamidopropylamine oxide, glycerin, fragrance, citric acid, tetrasodium EDTA, benzophenone-4, sodium benzoate, blue 1, red 33

Adverse reactions

INDEPENDANTLY TESTED • SATISFACTION GUARANTEED

If for any reason you are not satisfied with this product, please return it to the store where purchased for a full refund.

Distributed by: Pharmacy Value Alliance, LLC

407 East Lancaster Avenue,

Wayne, PA 19087

Principal display panel

Premier Value®

Foaming

Hand Wash

antibacterial

Fresh scent

INDEPENDENTLY TESTED

SATISFACTION GUARANTEED

7.5 FL OZ (221 mL)